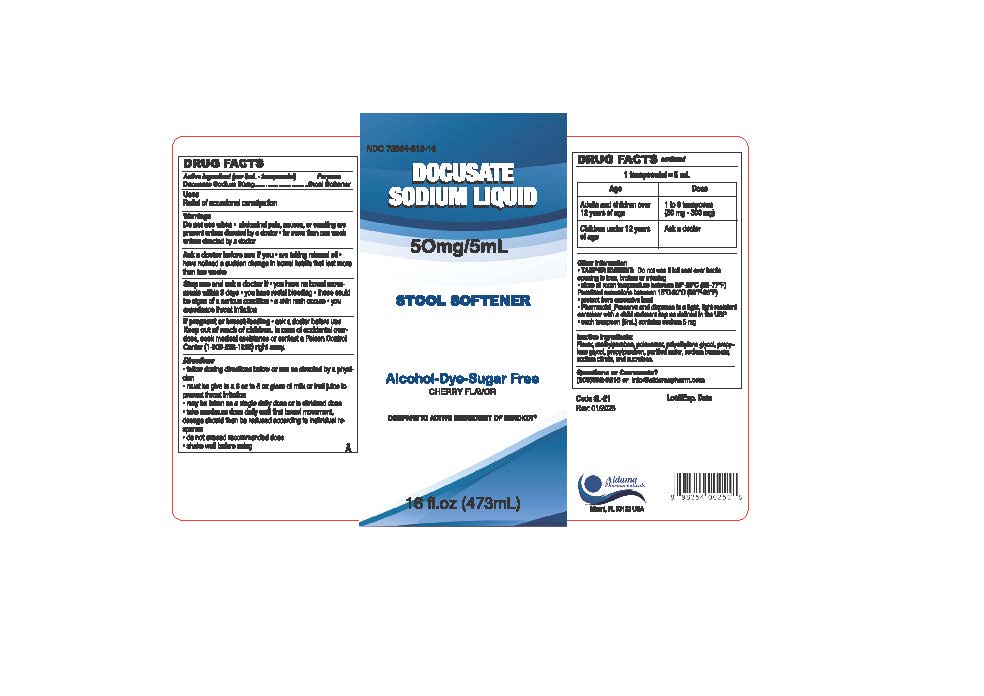 DRUG LABEL: Docusate Sodium Liquid
NDC: 73564-813 | Form: SOLUTION
Manufacturer: Aldama Pharmaceuticals, Inc
Category: otc | Type: HUMAN OTC DRUG LABEL
Date: 20260124

ACTIVE INGREDIENTS: DOCUSATE SODIUM 50 mg/5 mL
INACTIVE INGREDIENTS: SODIUM BENZOATE; POLOXAMER 124; WATER; SUCRALOSE; PROPYLENE GLYCOL; METHYLPARABEN; PROPYLPARABEN; SODIUM CITRATE; POLYETHYLENE GLYCOL 500

Docusate Sodium Liquid

Active ingredient (in each 5 mL-teaspoonful)

Docusate Sodium 50mg

Purpose

Stool Softener

Uses

- Relief of occasional constipation

Warnings

- abdominal pain, nauseas, or vomiting are present unless directed by a doctor
- for more than one week unless directed by a doctor

Do not use

- abdominal pain, nauseas, or vomiting are present unless directed by a doctor
- for more than one week unless directed by a doctor

Ask a doctor before use if you

- are taking mineral oil
- have noticed a sudden change in bowel habits that last more than two weeks

Stop use and ask a doctor if

- you have no bowel movements withing 3 days
- you have rectal bleeding
- these could be signs of a seriuos condition
- a skin rash occurs
- you experience throat irritation

If pregnant or breast-feeding

ask a doctor before use

Keep out of reach of children.

In case of overdose, seek medical assistance or contact a Poison Control Center (1-800-222-1222) right away.

Directions

- follow dosing directions below or use as directed by a physician
- must be give in a 6 oz to 8 oz glass of mil or fruit juice to prevent throat irritation
- may be taken as a single daily dose or in dividend dose
- take maximum dose daily until first bowel movement dosage should the be reduced according to individual response
- do not exceed recommende dose
- shake well before using

Other information

- TAMPER EVIDENT: Do not use if foil seal over bottle opening is torn, broken or missing
- store at room temperature between 20-25°C (68-77°F)
- Permitted excursions between 15-30°C (59-86°F)
- protect from excessive heat
- Pharmacist:: preserve and dispense in a tight light, light-resistant container with a child-resistant cap as defined in the UPS
- each teaspoon (5ml) contains sodium 5 mg

Inactive Ingredient

artificial and natural cherry flavor, citric acid, methylparaben, propylene glycol, propylparaben, purified water, sodium citrate, sucralose

Question or Comments?

305-592-9216 or info@aldamapharm.com